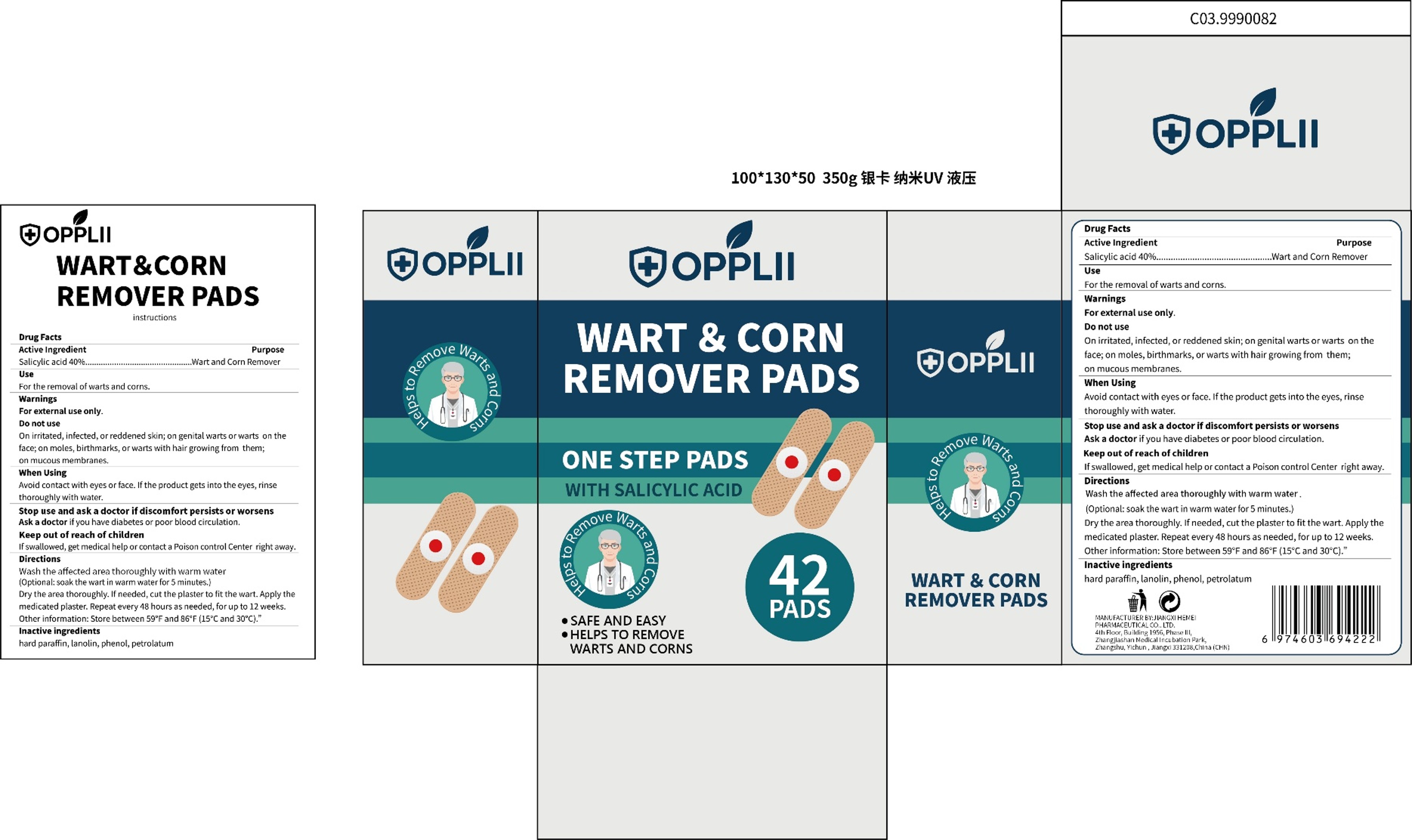 DRUG LABEL: WART CORN REMOVER
NDC: 85825-002 | Form: PATCH
Manufacturer: Shenzhen Haizhida E-commerce Co., Ltd
Category: otc | Type: HUMAN OTC DRUG LABEL
Date: 20250625

ACTIVE INGREDIENTS: SALICYLIC ACID 0.4 g/1 1
INACTIVE INGREDIENTS: PHENOL; LANOLIN; PARAFFIN; PETROLATUM

85825-002 WART CORN REMOVER

ACTIVE INGREDIENT

Salicylic acid 40%

PURPOSE

Wart and Corn Remover

INDICATIONS AND USAGE

For the removal of warts and corns.

WARNINGS

For external use only.

DO NOT USE

On irritated, infected, or reddened skin; on genital warts or warts on theface; on moles, birthmarks, or warts with hair growing from them;on mucous membranes.

WHEN USING

Avoid contact with eyes or face. lf the product gets into the eyes, rinse
thoroughly with water.

Stop use and ask a doctorif discomfort persists or worsens
Ask a doctor if you have diabetes or poor blood circulation.

KEEP OUT OF REACH OF CHILDREN

lf swallowed, get medical help or contact a Poison control Center right away.

DOSAGE AND ADMINISTRATION

Wash the affected area thoroughly with warm water (Optional: soak the wart in warm water for 5 minutes.)
Dry the area thoroughly. lf needed, cut the plaster to fit the wart. Apply the medicated plaster, Repeat every 48 hours as needed, for up to 12 weeks. Other information: Store between 59'F and 86°F(15°c and 30°C)."

INACTIVE INGREDIENT

Lanolin
Hard paraffin
Petrolatum
Phenol